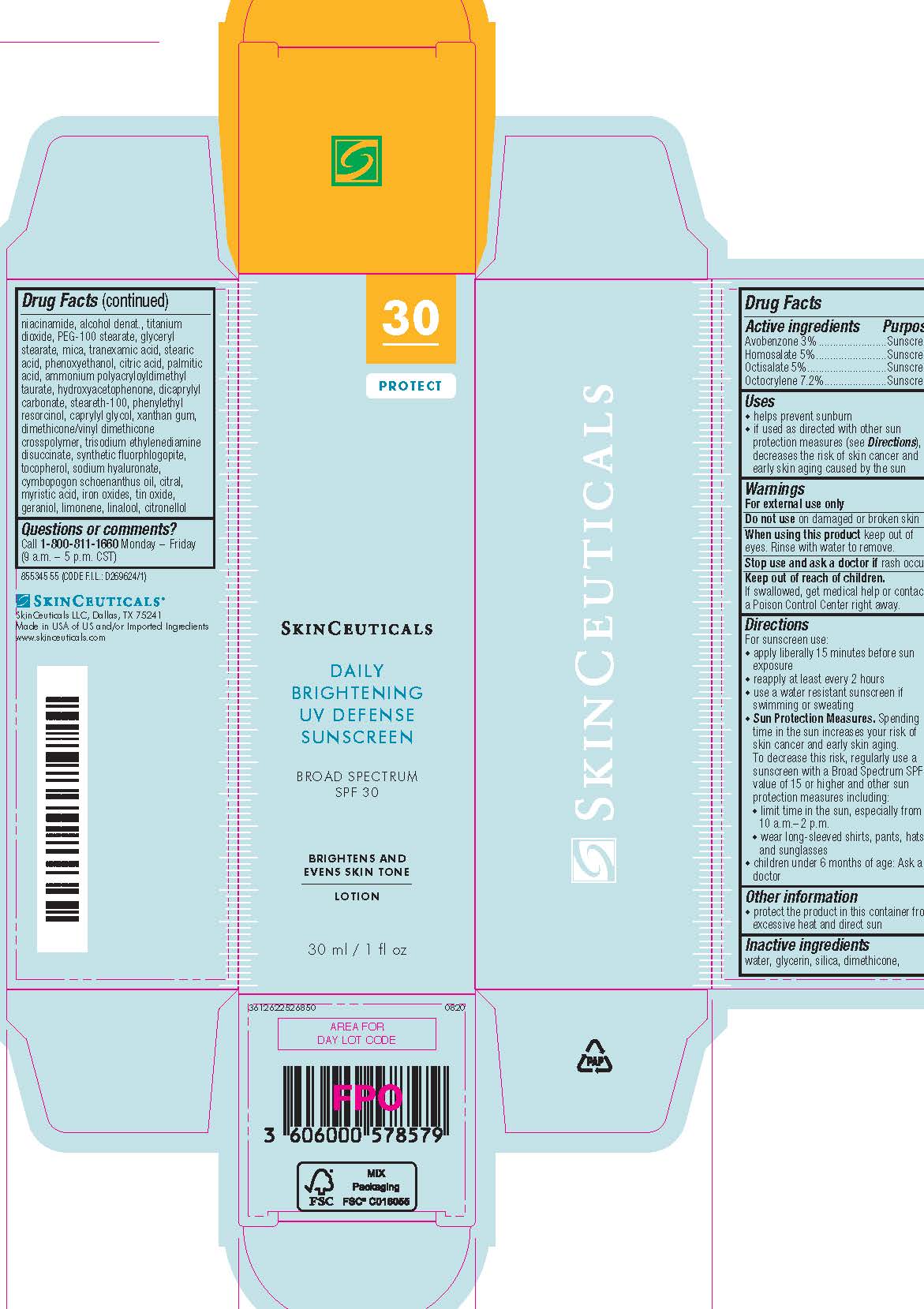 DRUG LABEL: SkinCeuticals Daily Brightening UV Defense Broad Spectrum SPF 30 Sunscreen
NDC: 49967-861 | Form: LOTION
Manufacturer: L'Oreal USA Products Inc
Category: otc | Type: HUMAN OTC DRUG LABEL
Date: 20231228

ACTIVE INGREDIENTS: AVOBENZONE 30 mg/1 mL; HOMOSALATE 50 mg/1 mL; OCTISALATE 50 mg/1 mL; OCTOCRYLENE 72 mg/1 mL
INACTIVE INGREDIENTS: WATER; GLYCERIN; SILICON DIOXIDE; DIMETHICONE; NIACINAMIDE; ALCOHOL; TITANIUM DIOXIDE; PEG-100 STEARATE; GLYCERYL MONOSTEARATE; MICA; TRANEXAMIC ACID; STEARIC ACID; PHENOXYETHANOL; CITRIC ACID MONOHYDRATE; PALMITIC ACID; AMMONIUM POLYACRYLOYLDIMETHYL TAURATE (55000 MPA.S); HYDROXYACETOPHENONE; DICAPRYLYL CARBONATE; STEARETH-100; PHENYLETHYL RESORCINOL; CAPRYLYL GLYCOL; XANTHAN GUM; DIMETHICONE/VINYL DIMETHICONE CROSSPOLYMER (SOFT PARTICLE); TRISODIUM ETHYLENEDIAMINE DISUCCINATE; TOCOPHEROL; HYALURONATE SODIUM; CYMBOPOGON SCHOENANTHUS OIL; CITRAL; MYRISTIC ACID; FERRIC OXIDE RED; STANNIC OXIDE; GERANIOL; LIMONENE, (+)-; LINALOOL, (+/-)-; .BETA.-CITRONELLOL, (R)-

Drug Facts

Active ingredients

Avobenzone 3%

Homosalate 5%

Octisalate 5%

Octocrylene 7.2%

Purpose

Sunscreen

Uses

- helps prevent sunburn

- if used as directed with other sun protection measures (see Directions), decreases the risk of skin cancer and early skin aging caused by the sun

Warnings

For external use only

Do not use

on damaged or broken skin

When using this product

keep out of eyes. Rinse with water to remove.

Stop use and ask a doctor if

rash occurs

Keep out of reach of children.

If swallowed, get medical help or contact a Poison Control Center right away.

Directions

● apply liberally 15 minutes before sun exposure

● reapply at least every 2 hours

● use a water resistant sunscreen if swimming or sweating

● Sun Protection Measures. Spending time in the sun increases your risk of skin cancer and early skin aging. To decrease this risk,

regularly use a sunscreen with a Broad Spectrum SPF value of 15 or higher and other sun protection measures including:

● limit time in the sun, especially from 10 a.m. – 2 p.m.

● wear long-sleeved shirts, pants, hats, and sunglasses

● children under 6 months of age: Ask a doctor

Other information

protect the product in this container from excessive heat and direct sun

Inactive ingredients

water, glycerin, silica, dimethicone, niacinamide, alcohol denat., titanium dioxide, PEG-100 stearate, glyceryl stearate, mica, tranexamic acid, stearic acid, phenoxyethanol, citric acid, palmitic acid, ammonium polyacryloyldimethyl taurate, hydroxyacetophenone, dicaprylyl carbonate, steareth-100, phenylethyl resorcinol, caprylyl glycol, xanthan gum, dimethicone/vinyl dimethicone crosspolymer, trisodium ethylenediamine disuccinate, synthetic fluorphlogopite, tocopherol, sodium hyaluronate, cymbopogon schoenanthus oil, citral, myristic acid, iron oxides, tin oxide, geraniol, limonene, linalool, citronellol

Questions or comments?

Call 1-800-811-1660

Monday - Friday (9 a.m. - 5 p.m. CST)